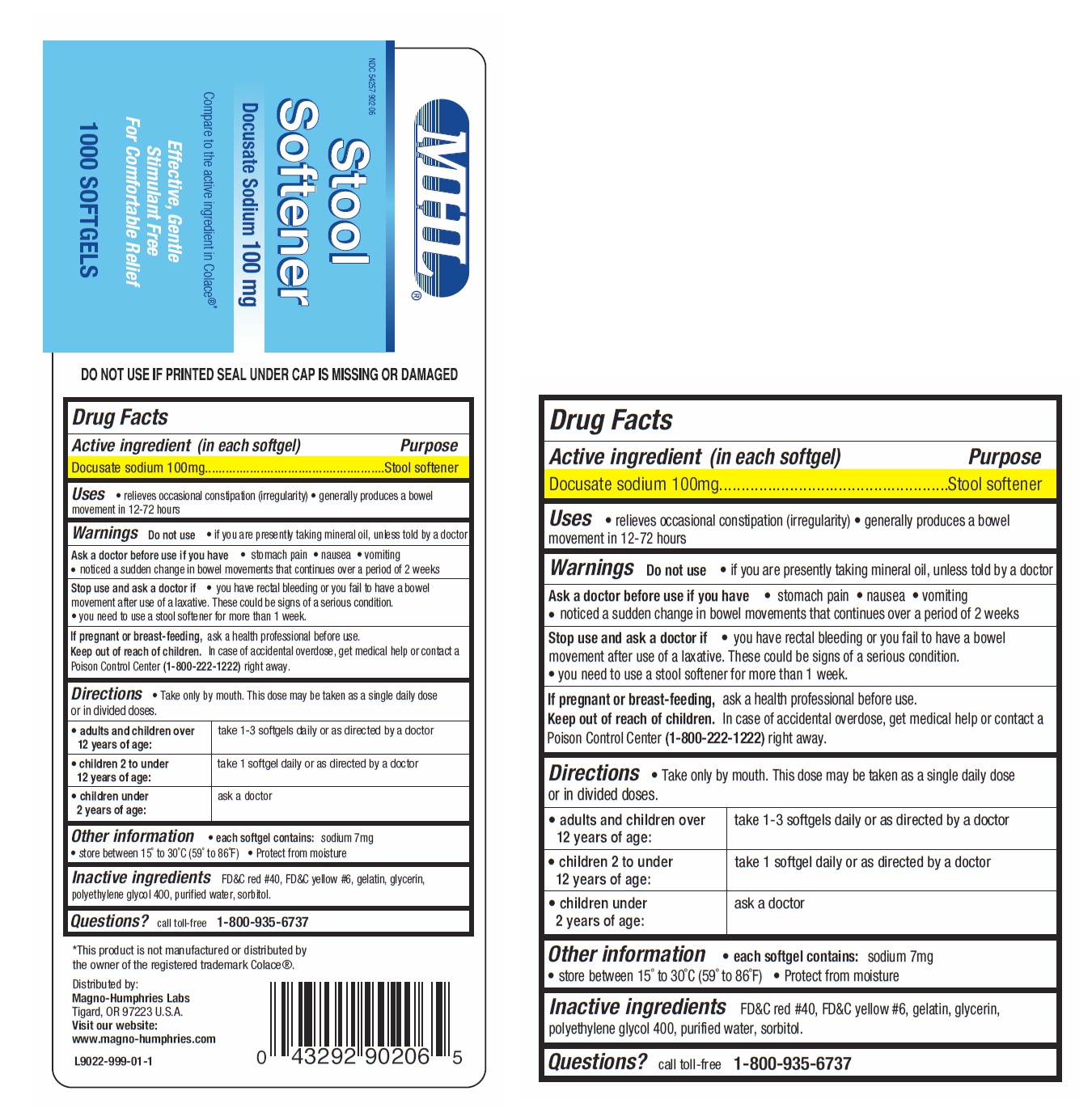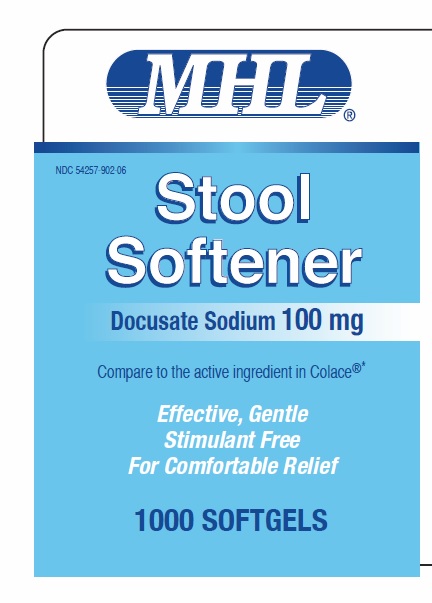 DRUG LABEL: Stool Softener Docusate Sodium
NDC: 54257-902 | Form: CAPSULE, GELATIN COATED
Manufacturer: Magno-Humphries, Inc.
Category: otc | Type: HUMAN OTC DRUG LABEL
Date: 20231027

ACTIVE INGREDIENTS: DOCUSATE SODIUM 100 mg/1 1
INACTIVE INGREDIENTS: GELATIN, UNSPECIFIED; GLYCERIN; POLYETHYLENE GLYCOL 400; WATER; SORBITOL

Stool Softener Docusate Sodium

MHL NDC 54257-902-06

Stool Softener Docusate Sodium 100mg Compare to the active ingredient in Colace *
®

Effective, Gentle Stimulant Free For Comfortable Relief

1000 SOFTGELS

Active ingredient (in each softgel)

Docusate sodium 100mg

Purpose

Stool softener

Uses

- relieves occasional constipation (irregularity)
- generally produces a bowel movement in 12-72 hours

Warnings

Do not use

Ask a doctor before use if you have

Stop use and ask a doctor if

ask a health professional before use. If pregnant or breast-feeding,

- if you are presently taking mineral oil, unless told by a doctor

- stomach pain
- nausea
- vomiting
- noticed a sudden change in bowel movements that continues over a period of 2 weeks

- you have rectal bleeding or you fail to have a bowel movement after use of a laxative. These could be signs of a serious condition.
- you need to use a stool softener for mroe than 1 week.

Keep out of reach of children.

In case of accidental overdose, get medical help or contact a Poison Control Center () right away. 1-800-222-1222

Directions

- Take only by mouth. This dose may be taken as a single daily dose or in divided doses.
- take 1-3 softgels daily or as directed by a doctor adults and children over 12 years of age:
- take 1 softgel daily or as directed by a doctor children 2 to under 12 years of age:
- ask a doctor children under 2 years of age:

Other information

- sodium 7mg each softgel contains:
- store between 15° to 30°C (59° to 86°F)
- Protect from moisture

Inactive ingredients

FD&C red #40, FD&C yellow #6, gelatin, glycerin, polyethylene glycol 400, purified water, sorbitol.

Questions?

call toll-free 1-800-935-6737

*This product is not manufactured or distributed by the owner of the registered trademark Colace®. Distributed by: Magno-Humphries, Inc. OR 97223 U.S.A. Visit our website: www.magno-humphries.com

*This product is not manufactured or distributed by the owner of the registered trademark Colace®.

Distributed by: , OR 97223 U.S.A.
Magno-Humphries, Inc.Visit our website: www.magno-humphries.com